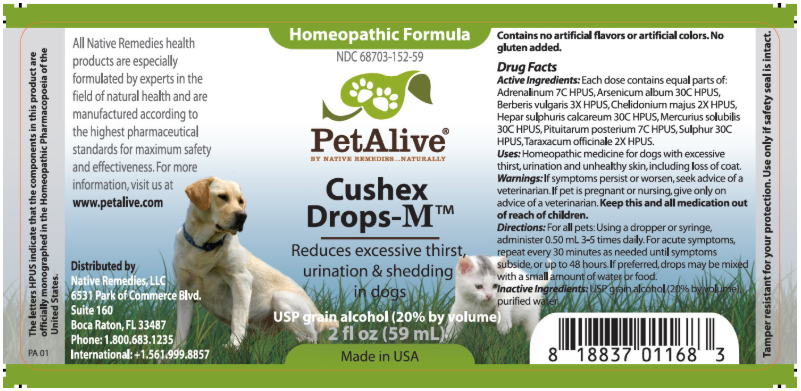 DRUG LABEL: Cushex Drops-M
NDC: 68703-152 | Form: TINCTURE
Manufacturer: SILVER STAR BRANDS
Category: homeopathic | Type: OTC ANIMAL DRUG LABEL
Date: 20251118

ACTIVE INGREDIENTS: EPINEPHRINE 7 [hp_C]/1 mL; ARSENIC TRIOXIDE 30 [hp_C]/1 mL; BERBERIS VULGARIS ROOT BARK 3 [hp_X]/1 mL; CHELIDONIUM MAJUS 2 [hp_X]/1 mL; CALCIUM SULFIDE 30 [hp_C]/1 mL; MERCURIUS SOLUBILIS 30 [hp_C]/1 mL; SUS SCROFA PITUITARY GLAND, POSTERIOR 7 [hp_C]/1 mL; SULFUR 30 [hp_C]/1 mL; TARAXACUM OFFICINALE 2 [hp_X]/1 mL
INACTIVE INGREDIENTS: ALCOHOL; WATER

Cushex Drops-M

PURPOSE

Reduce excessive thirst, urination and shedding in dogs

Drug Facts
Active Ingredients: Each dose contains equal parts of: Adrenalinum 7C HPUS, Arsenicum album 30C HPUS, Berberis vulgaris 3X HPUS, Chelidonium majus 2X HPUS, Hepar sulphuris calcareum 30C HPUS, Mercuris solubilis 30C HPUS, Pituitarum posterium 7C HPUS, Sulphur 30C HPUS, Tarazacum officinale 2X HPUS

INDICATIONS AND USAGE

Uses: Homeopathic medicine for dogs with excessive thirst, urination and unhealthy skin, including loss of coat

WARNINGS

Warnings:If symptoms persist or worsen, seek advice of a veterinarian

PREGNANCY OR BREAST FEEDING

If pet is pregnant or nursing, give only on advice of a veterinarian

KEEP OUT OF REACH OF CHILDREN

Keep this and all medication out of reach of children

DOSAGE AND ADMINISTRATION

Directions:For all pets: Using a dropper or syringe, administer 0.50 mL 3-5 times daily. For acute symptoms, repeat every 30 minutes as needed until symptoms subside, or up to 48 hours. If preferred, drops may be mixed with a small amount of water or food

INACTIVE INGREDIENT

Inactive Ingredients: USP grain alcohol (20% by volume), purified water

INFORMATION FOR OWNERS/CAREGIVERS

The letters HPUS indicate that the components in this product are officially monographed in the Homeopathic Pharmacopoeia of the United States

All Native Remedies health products are especially formulated by experts in the fields of natural health and are manufactured according to the highest pharmaceutical standards for maximum safety and effectiveness. For more information, visit us at www.petalive.com

Distributed by
Native Remedies, LLC
6531 Park of Commerce Blvd.
Suite 160
Boca Raton, Fl 33487
Phone: 1.800.683.1235
International : +1.561.999.8857

Contains no artificial flavors or artificial colors. No gluten added

STORAGE AND HANDLING

Tamper resistant for your protection, Use only if safety seal is intact